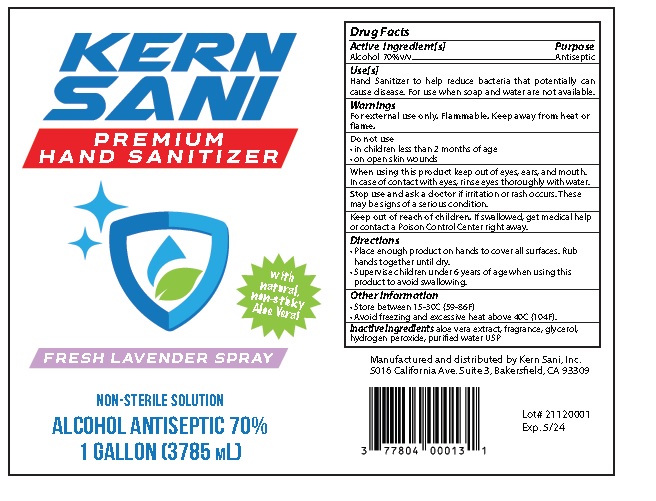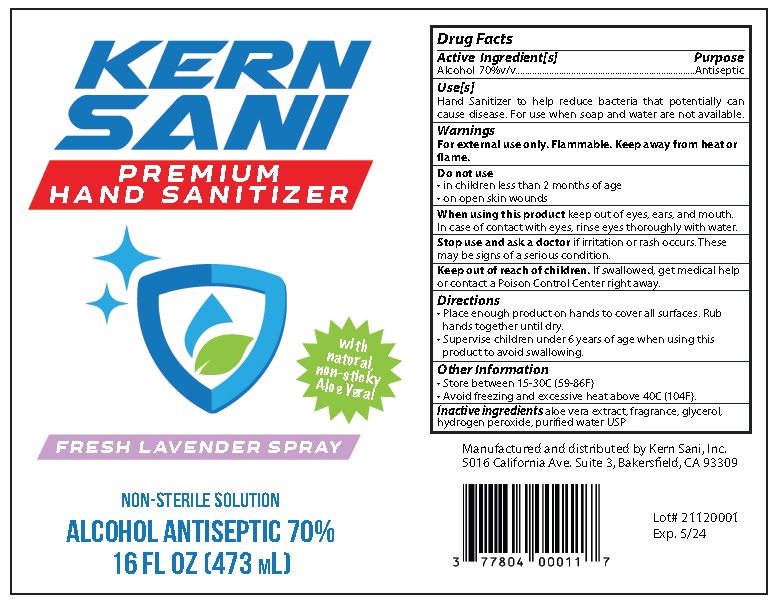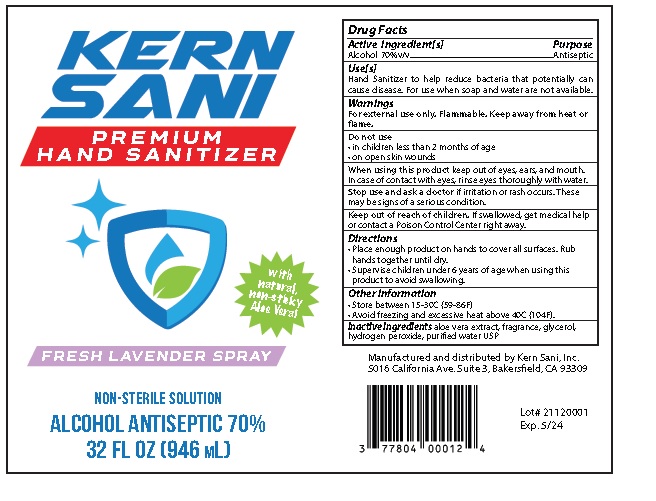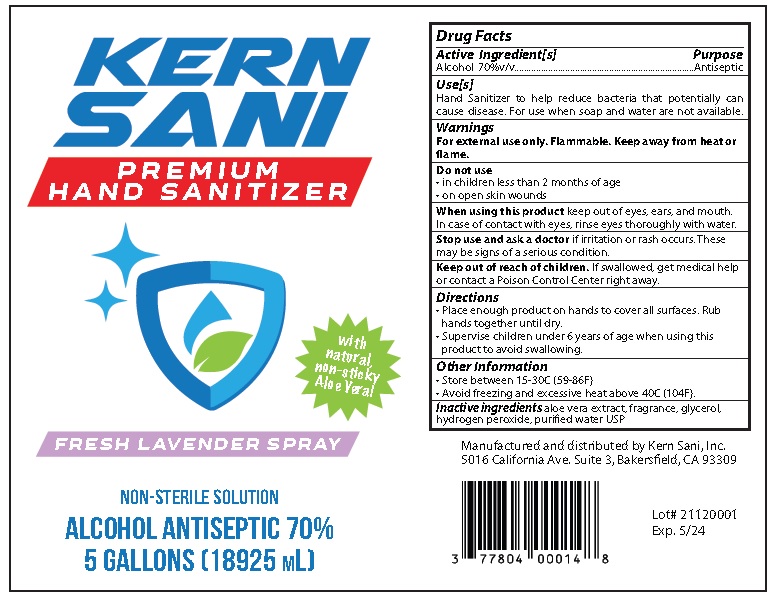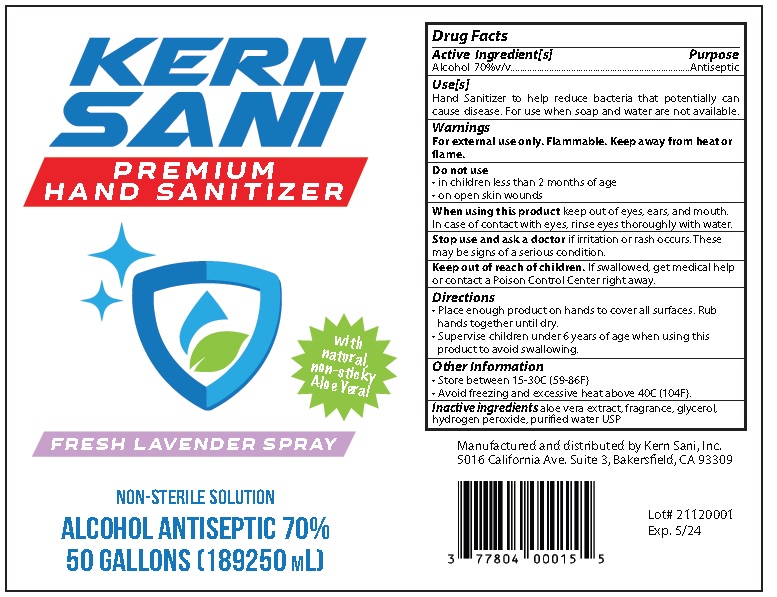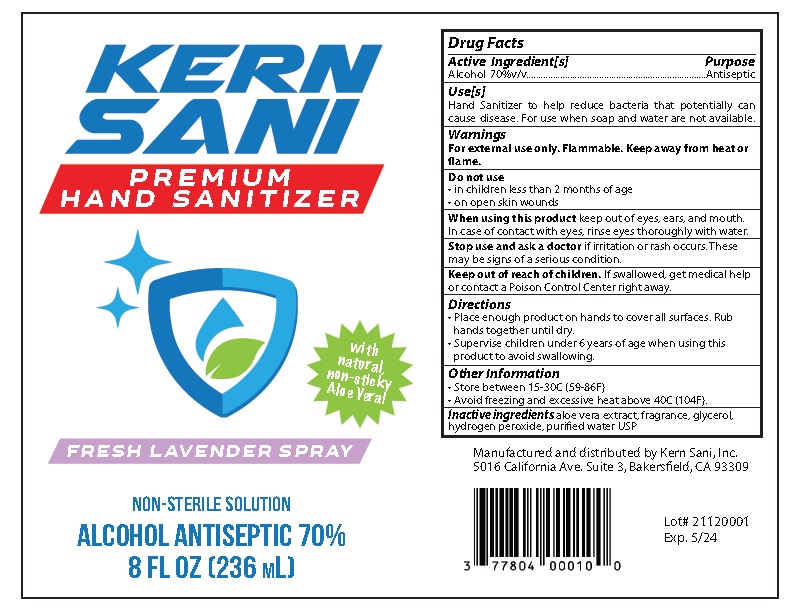 DRUG LABEL: Premium Hand Sanitizer Fresh Lavender
NDC: 77804-008 | Form: SOLUTION
Manufacturer: KERN SANI, INC.
Category: otc | Type: HUMAN OTC DRUG LABEL
Date: 20210612

ACTIVE INGREDIENTS: ALCOHOL 70 mL/100 mL
INACTIVE INGREDIENTS: ALOE VERA LEAF; GLYCERIN; HYDROGEN PEROXIDE; WATER

KERN SANI Premium Hand Sanitizer Fresh Lavender Spray

Drug Facts

Active Ingredient[s]

Alcohol 70%v/v

Purpose

Antiseptic

INDICATIONS AND USAGE

Use[s]

Hand Sanitizer to help reduce bacteria that potentially can cause disease. For use when soap and water are not available.

Warnings

For external use only. Flammable. Keep away from heat or flame

Do not use

- in children less than 2 months of age

- on open skin wounds

When using this product keep out of eyes, ears, and mouth. In case of contact with eyes, rinse eyes thoroughly with water.

Stop use and ask a doctor if irritation or rash occurs. These may be signs of a serious condition.

Keep out of reach of children. If swallowed, get medical help or contact a Poison Control Center right away.

Directions

- Place enough product on hands to cover all surfaces. Rub hands together until dry.

- Supervise children under 6 years of age when using this product to avoid swallowing.

Other information

- Store between 15-30C (59-86F)

- Avoid freezing and excessive heat above 40C (104F)

Inactive ingredients aloe vera extract, fragrance, glycerol,

hydrogen peroxide, purified water

Principal Display Package

KERN

SANI

PREMIUM

HAND SANITIZER

FRESH LAVENDER SPRAY

NON-STERILE SOLUTION

ALCOHOL ANTISEPTIC 70%

8 FL OZ (236 mL)

Manufactured and distributed by Kern Sani Inc.

5016 California Ave. Suite3, Bakersfield, CA 93309

Lot#

Exp.

8 Oz. Lavender spray

16 Oz. Lavender spray

32 Oz. Lavender spray

1 gal

5 gal

50 gal

res